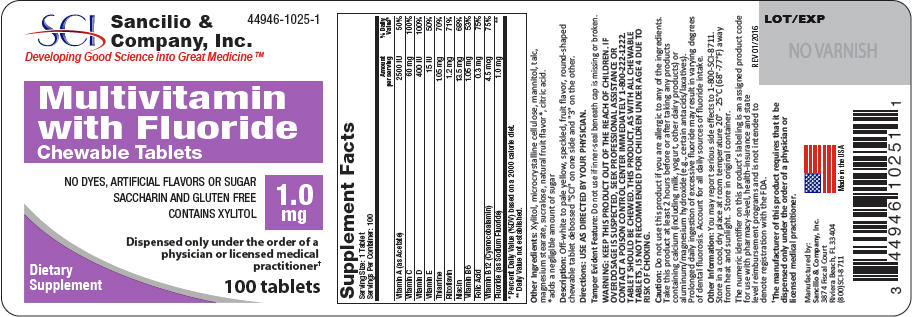 DRUG LABEL: Multivitamin with fluoride
NDC: 44946-1025 | Form: TABLET, CHEWABLE
Manufacturer: Sancilio & Company Inc
Category: other | Type: DIETARY SUPPLEMENT
Date: 20180302

ACTIVE INGREDIENTS: .Alpha.-Tocopherol Acetate, DL- 15 [iU]/1 1; Ascorbic Acid 60 mg/1 1; Cyanocobalamin 4.5 ug/1 1; Sodium Fluoride 1 mg/1 1; Folic Acid 0.3 mg/1 1; Niacin 13.5 mg/1 1; Pyridoxine 1.05 mg/1 1; Riboflavin 1.2 mg/1 1; Thiamine 1.05 mg/1 1; Vitamin A 2500 [iU]/1 1; Vitamin D 400 [iU]/1 1
INACTIVE INGREDIENTS: Xylitol; microcrystalline cellulose; Mannitol; Talc; Magnesium stearate; Sucralose; Anhydrous Citric acid

Multivitamin with Fluoride
Chewable Tablets

HEALTH CLAIM

Each Multivitamin with 1.0 mg Fluoride Tablet Contains:
Vitamin A (as Acetate) | 2500 IU
Vitamin C | 60 mg
Vitamin D | 400 IU
Vitamin E | 15 IU
Thiamine | 1.05 mg
Riboflavin | 1.2 mg
Niacin | 13.5 mg
Vitamin B6 | 1.05 mg
Folate (as Folic Acid) | 0.3 mg
Vitamin B12 | 4.5 mcg
Fluoride (as Sodium Fluoride) [Each Multivitamin with 1.0 mg Fluoride Tablet contains 1.0 mg Fluoride from 2.2 mg Sodium Fluoride (NaF).] | 1.0 mg

WARNING

KEEP THIS AND ALL MEDICATIONS OUT OF THE REACH OF CHILDREN. IF OVERDOSAGE IS SUSPECTED, SEEK PROFESSIONAL ASSISTANCE OR CONTACT A POISON CONTROL CENTER IMMEDIATELY 1-800-222-1222. TABLET SHOULD BE CHEWED. THIS PRODUCT, AS WITH ALL CHEWABLE TABLETS, IS NOT RECOMMENDED FOR CHILDREN UNDER AGE 4 DUE TO RISK OF CHOKING.

DO NOT USE IF FOIL SEAL UNDER CAP IS BROKEN OR MISSING

Directions

USE AS DIRECTED BY YOUR PHYSICIAN.

Description

Off-white to pale yellow, speckled, fruit flavor, round-shaped chewable tablet debossed "SCI" on one side and "3" on the other.

Caution

Do not use this product if you are allergic to any of the ingredients. Take this product at least 2 hours before or after taking any products containing calcium (including milk, yogurt, other dairy products) or aluminum/magnesium hydroxide (e.g., certain antacids/laxatives). Prolonged daily ingestion of excessive fluoride may result in varying degrees of dental fluorosis. Account for all daily sources of fluoride intake.

Other Ingredients

Xylitol, microcrystalline cellulose, mannitol, talc, magnesium stearate, sucralose, natural fruit flavor, citric acid.

Storage

Store in a cool, dry place at room temperature 20° - 25°C (68° - 77°F) away from heat and sunlight. Store in original container.

HEALTH CLAIM

This medical food product is formulated to be administered orally, under the ongoing supervision of a physician and is intended for the dietary management of dental caries for which a distinctive nutritional requirement of fluoride, based on recognized scientific principles, has been established by medical evaluation.

The numeric identifier on this product's labeling is an assigned product code for use with pharmacy-level, health-insurance and state level reimbursement programs and is not intended to denote registration with the FDA.

Manufactured by: Sancilio & Co., Inc. Riviera Beach, FL 33404 USA

rev. 11/18/11

PRINCIPAL DISPLAY PANEL - 1.0 mg Tablet Bottle Label

Sancilio &
Company, Inc.
Developing Good Science into Great Medicine ™

44946-1025-1

Multivitamin
with Fluoride
Chewable Tablets

NO DYES, ARTIFICIAL FLAVORS OR SUGAR
SACCHARIN AND GLUTEN FREE
CONTAINS XYLITOL

1.0
mg

Dispensed only under the order of a
physician or licensed medical
practitioner†

Dietary
Supplement

100 tablets